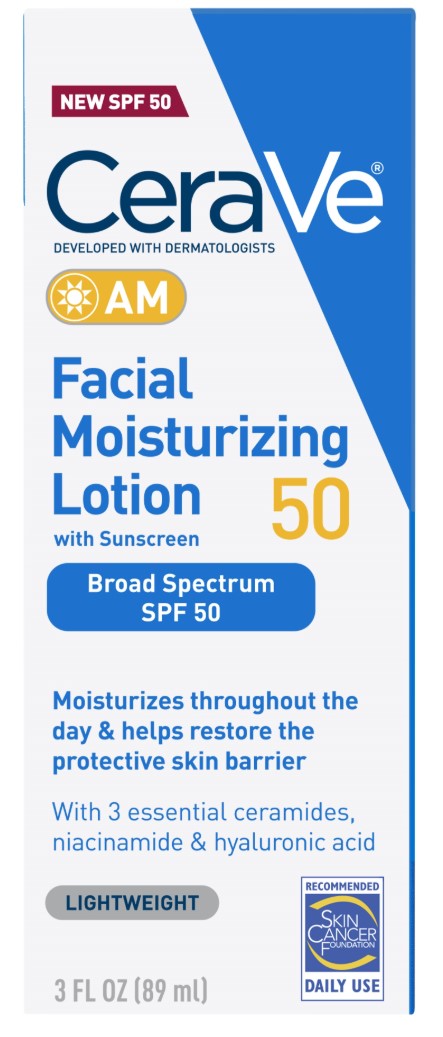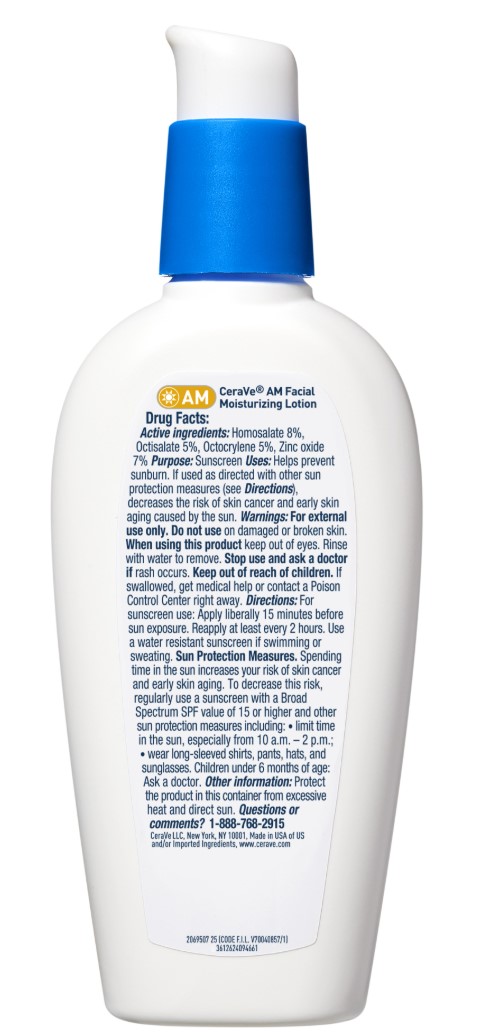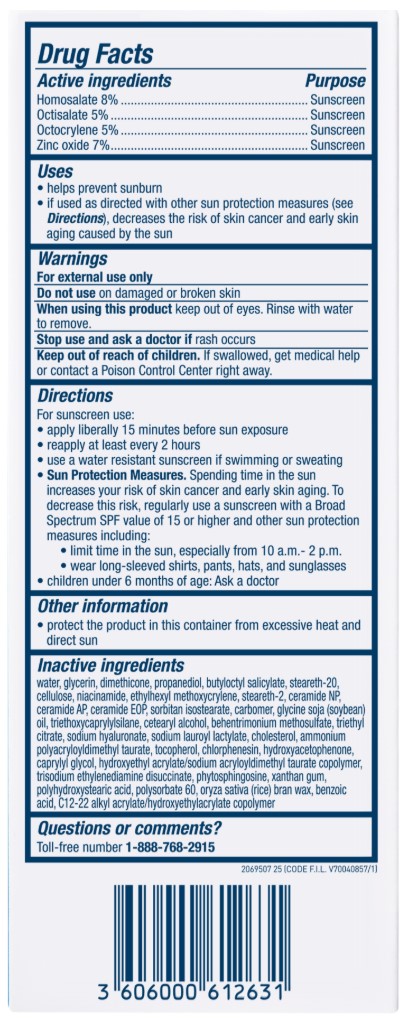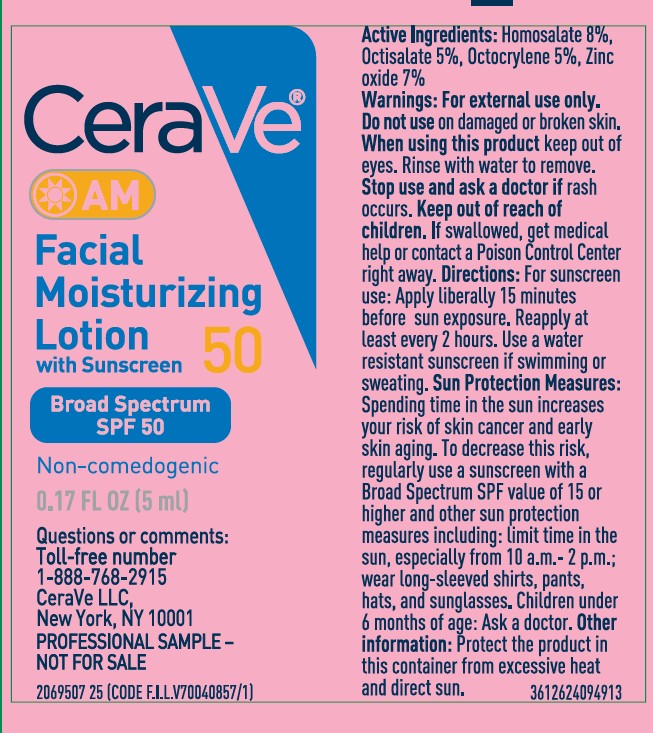 DRUG LABEL: CeraVe AM Facial Moisturizing Broad Spectrum SPF 50 Sunscreen
NDC: 49967-263 | Form: LOTION
Manufacturer: L'Oreal USA Products Inc
Category: otc | Type: HUMAN OTC DRUG LABEL
Date: 20250328

ACTIVE INGREDIENTS: HOMOSALATE 80 mg/1 mL; OCTISALATE 50 mg/1 mL; OCTOCRYLENE 50 mg/1 mL; ZINC OXIDE 70 mg/1 mL
INACTIVE INGREDIENTS: WATER; GLYCERIN; DIMETHICONE; PROPANEDIOL; BUTYLOCTYL SALICYLATE; STEARETH-20; POWDERED CELLULOSE; NIACINAMIDE; ETHYLHEXYL METHOXYCRYLENE; STEARETH-2; CERAMIDE NP; CERAMIDE AP; CERAMIDE 1; SORBITAN ISOSTEARATE; CARBOMER HOMOPOLYMER, UNSPECIFIED TYPE; SOYBEAN OIL; TRIETHOXYCAPRYLYLSILANE; CETOSTEARYL ALCOHOL; BEHENTRIMONIUM METHOSULFATE; TRIETHYL CITRATE; HYALURONATE SODIUM; SODIUM LAUROYL LACTYLATE; CHOLESTEROL; AMMONIUM POLYACRYLOYLDIMETHYL TAURATE; TOCOPHEROL; CHLORPHENESIN; HYDROXYACETOPHENONE; CAPRYLYL GLYCOL; HYDROXYETHYL ACRYLATE/SODIUM ACRYLOYLDIMETHYL TAURATE COPOLYMER (45000 MPA.S AT 1%); TRISODIUM ETHYLENEDIAMINE DISUCCINATE; PHYTOSPHINGOSINE; XANTHAN GUM; POLYHYDROXYSTEARIC ACID STEARATE; POLYSORBATE 60; RICE BRAN; BENZOIC ACID

Drug Facts

Active ingredients

Homosalate 8%

Octisalate 5%

Octocrylene 5%

Zinc oxide 7%

Purpose

Sunscreen

Uses

- helps prevent sunburn
- if used as directed with other sun protection measures (see Directions), decreases the risk of skin cancer and early skin aging caused by the sun

Warnings

For external use only

Do not use

on damaged or broken skin

When using this product

keep out of eyes. Rinse with water to remove.

Stop use and ask a doctor if

rash occurs

Keep out of reach of children.

If swallowed, get medical help or contact a Poison Control Center right away.

Directions

For sunscreen use:

- apply liberally 15 minutes before sun exposure
- reapply at least every 2 hours
- use a water resistant sunscreen if swimming or sweating
- Sun Protection Measures. Spending time in the sun increases our risk of skin cancer and early skin aging. To decrease this risk, regularly use a sunscreen with a Broad Spectrum SPF value of 15 or higher and other sun protection measures including:
- limit time in the sun, especially from 10 a.m. - 2 p.m.
- wear long-sleeved shirts, pants, hats, and sunglasses
- children under 6 months of age: Ask a doctor

Other information

- protect the product in this container from excessive heat and direct sun

Inactive ingredients

water, glycerin, dimethicone, propanediol, butyloctyl salicylate, steareth-20, cellulose, niacinamide, ehtylhexyl methoxycrylene, steareth-2, ceramide NP, ceramide AP, ceramide EOP, sorbitan isostearate, carbomer, glycine soja (soybean) oil, triethoxycaprylsilane, cetearyl alcohol, behentriminium methosulfate, triethyl citrate, sodium hyaluronate, sodium lauroryl lactylate, cholesterol, ammonium polyacryloyldimethyl taurate, tocopherol, chlorphenesin, hydroxyacetophenone, caprylyl glycol, hydroxyethyl acrylate/sodium acryloyldimethyl taurate copolymer, trisodium ethylenediamine disuccinate, phytosphingosine, xanthan gum, polyhydrostearic acid, polysorbate 60, oryza sativa (rice) bran wax, benzoic acid, c12-22 alkyl acrylate/hydroxyethylacrylate copolymer

Question or comments?

Toll-free number 1-877-768-2915